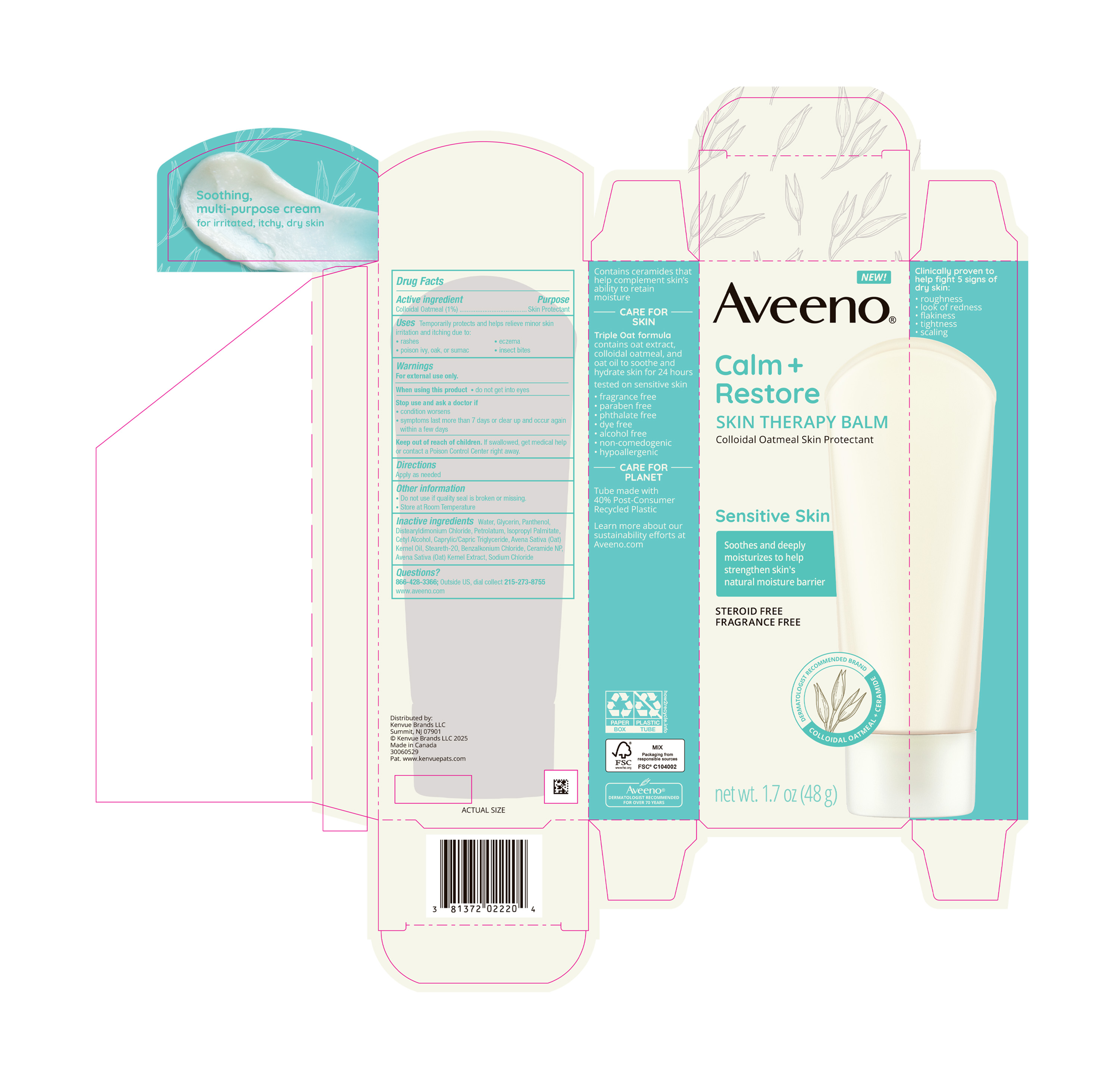 DRUG LABEL: Aveeno Calm Plus Restore Skin Therapy Balm
NDC: 69968-0755 | Form: CREAM
Manufacturer: Kenvue Brands LLC
Category: otc | Type: HUMAN OTC DRUG LABEL
Date: 20250604

ACTIVE INGREDIENTS: OATMEAL 10 mg/1 g
INACTIVE INGREDIENTS: BENZALKONIUM CHLORIDE; SODIUM CHLORIDE; PANTHENOL; ISOPROPYL PALMITATE; STEARETH-20; OAT KERNEL OIL; CERAMIDE NP; MEDIUM-CHAIN TRIGLYCERIDES; OAT; WATER; GLYCERIN; DISTEARYLDIMONIUM CHLORIDE; PETROLATUM; CETYL ALCOHOL

Aveeno Calm Plus Restore Skin Therapy Balm

Drug Facts

Active ingredient

Colloidal Oatmeal 1%

Purpose

Skin Protectant

Uses

Temporarily protects and helps relieve minor skin irritation and itching due to:

- rashes
- eczema
- poison ivy, oak, or sumac
- insect bites

Warnings

For external use only

When using this product

- Do not get into eyes

Stop use and ask a doctor if

- condition worsens
- symptoms last more than 7 days or clear up and occur again within a few days

Keep out of reach of children. If swallowed, get medical help or contact a Poison Control Center right away.

Directions

- Apply as needed.

Other information

- Do not use if quality seal is broken or missing.
- Store at Room Temperature

Inactive ingredients

Water, Glycerin, Panthenol, Distearyldimonium Chloride, Petrolatum, Isopropyl Palmitate, Cetyl Alcohol, Caprylic/Capric Triglyceride, Avena Sativa (Oat) Kernel Oil, Steareth-20, Benzalkonium Chloride, Ceramide NP, Avena Sativa (Oat) Kernel Extract, Sodium Chloride

Questions?

866-428-3366; Outside US, dial collect 215-273-8755

www.aveeno.com

Distributed by:
Kenvue Brands LLC
Summit, NJ 07901

PRINCIPAL DISPLAY PANEL - 48g Tube Carton

NEW!

Aveeno®

Calm +

Restore

SKIN THERAPY BALM

Colloidal Oatmeal Skin Protectant

Sensitive Skin

Soothes and deeply

moisturizes to help

strengthen skin’s

natural moisture barrier

STEROID FREE

FRAGRANCE-FREE

DERMATOLOGIST RECOMMENDED BRAND

COLLOIDAL OATMEAL + CERAMIDE

net wt. 1.7 oz (48 g)